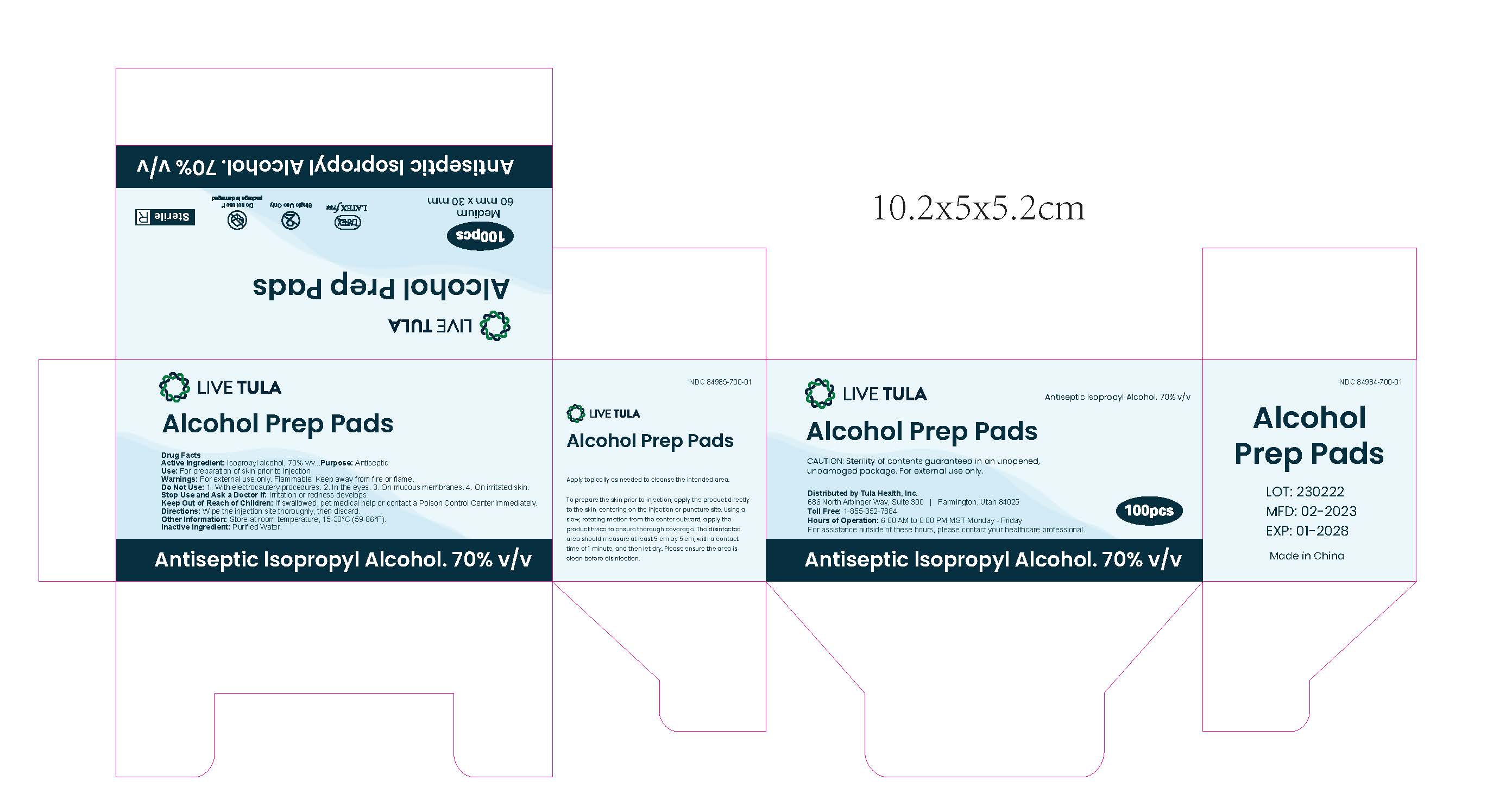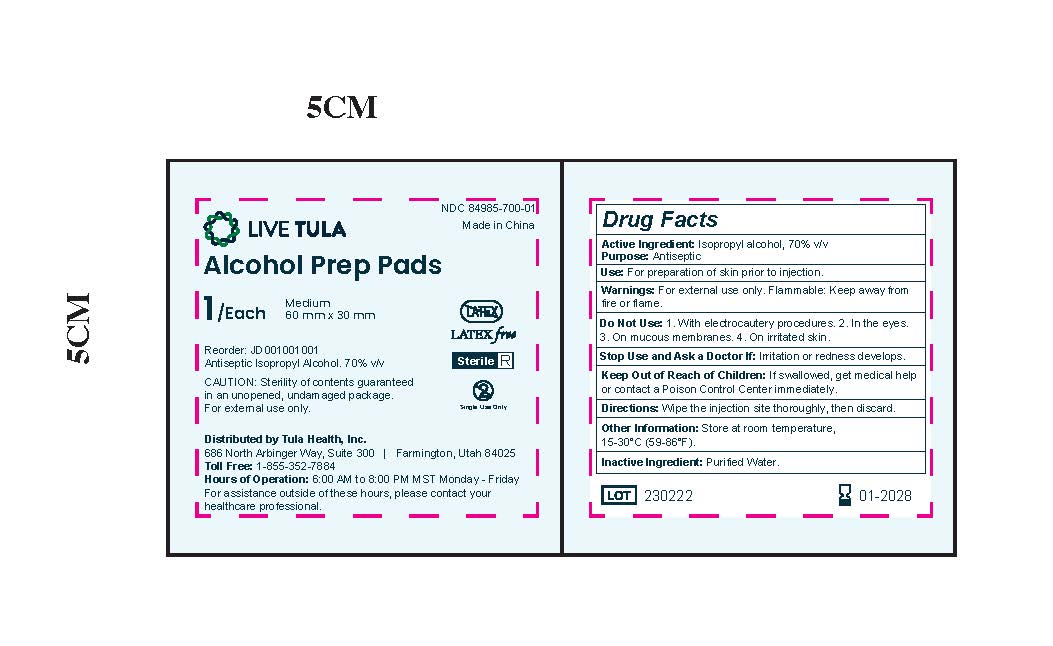 DRUG LABEL: LIVE TULA Alcohol Prep Pads Medium Sterile - Isopropyl Alcohol Wipes
NDC: 84985-700 | Form: CLOTH
Manufacturer: LIVE TULA, LLC
Category: otc | Type: HUMAN OTC DRUG LABEL
Date: 20250127

ACTIVE INGREDIENTS: ISOPROPYL ALCOHOL 70 mL/100 mL
INACTIVE INGREDIENTS: WATER 30 mL/100 mL

LIVE TULA DRUG LISTING AND CERTIFICATION

Drug Facts

Active Ingredient

Isopropyl Alcohol 70% v/v

Purpose

Antiseptic

Use

For preparation of the skin prior to injection to reduce the risk of infection.

Warnings
For external use only.

Flammable: Keep away from fire or flame.

Do not use

With electrocautery procedures.
In or near the eyes.
On mucous membranes.
On irritated or damaged skin.

Stop use and ask a doctor if

Irritation or redness develops.

Keep out of reach of children.

If swallowed, get medical help or contact a Poison Control Center right away.

Directions

1. Apply topically as needed to cleanse the intended area.
2. Use for skin preparation prior to injection:

Apply the product to the skin.
Take the injection or puncture site as the center, and slowly rotate outward in a circular motion.
Repeat application twice.
Ensure the disinfection area is at least 5cm x 5cm.
Allow a contact time of 1 minute for proper disinfection

3.Clean the area before disinfection, if necessary.

Other Information

Store at room temperature: 15–30°C (59–86°F).
Do not use the product if the packaging is damaged.

- Inactive Ingredient

Purified Water (UNII: 059QF0KO0R): 30 mL per 100 mL

Purified Water (used as a solvent).

DESCRIPTION

- Packaging Information

NDC Code: 84985-700-01

- Package Description:

100 prep pads per carton
Each pad contains 0.4 mL

- Product Information

Product Type: Human OTC Drug
Route of Administration: Topical

Active Ingredient/Strength

Isopropyl Alcohol (UNII: ND2M416302): 70 mL per 100 mL

DOSAGE AND ADMINISTRATION

Apply topically as needed to cleanse the intended area. Allow to dry before proceeding with the injection or procedure.

WARNINGS

Warnings: For external use only. Flammable: Keep away from fire or flame. Do not use: - With electrocautery procedures. - In the eyes, on mucous membranes, or on irritated skin. Stop use and ask a doctor if irritation or redness develops.

INDICATIONS AND USAGE

Indications & Usage: Use for preparation of the skin prior to injection to reduce the risk of infection.

Keep Out of Reach of Children: If swallowed, get medical help or contact a Poison Control Center right away.

Purpose: Antiseptic